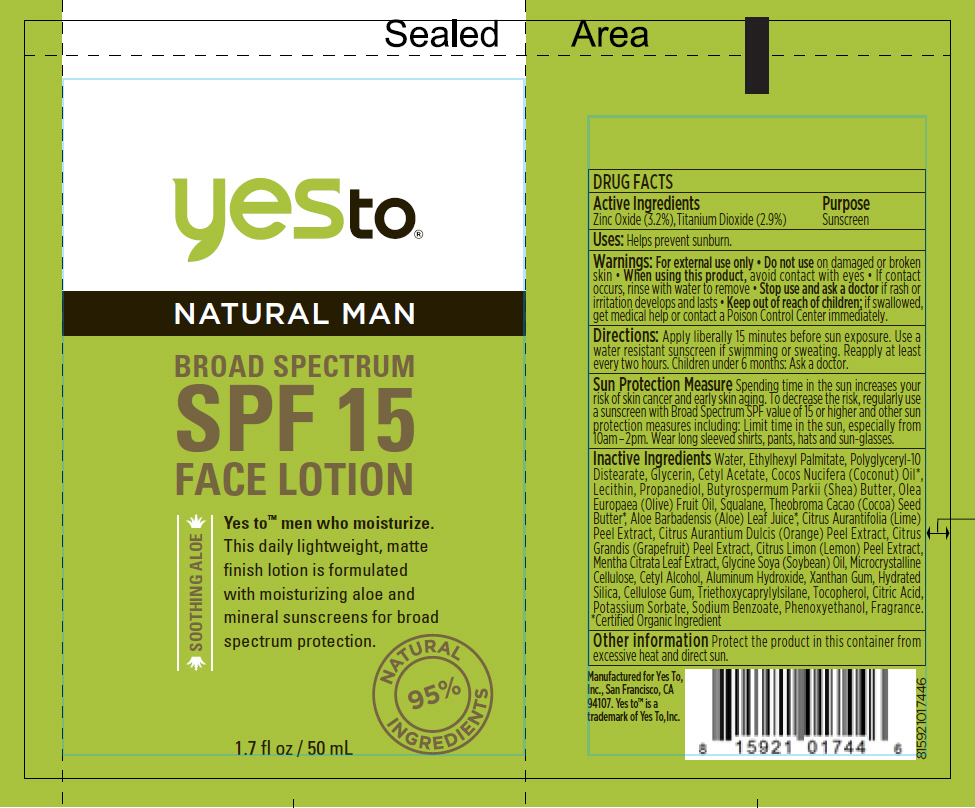 DRUG LABEL: Yes to Natural Man Broad Spectrum SPF 15 Face
NDC: 69840-006 | Form: CREAM
Manufacturer: Yes To Inc.
Category: otc | Type: HUMAN OTC DRUG LABEL
Date: 20151105

ACTIVE INGREDIENTS: Zinc Oxide 32 mg/1 mL; Titanium Dioxide 29 mg/1 mL
INACTIVE INGREDIENTS: Water; Ethylhexyl Palmitate; Polyglyceryl-10 Stearate; Glycerin; Cetyl Acetate; Propanediol; Egg Phospholipids; Coconut Oil; Shea Butter; Cocoa Butter; Olive Oil; Squalane; Phenoxyethanol; Cellulose, Microcrystalline; Cetyl Alcohol; Aluminum Hydroxide; Xanthan Gum; Hydrated Silica; Carboxymethylcellulose Sodium, Unspecified Form; Triethoxycaprylylsilane; Tocopherol; Aloe Vera Leaf; ORANGE; LIME PEEL; Mentha Aquatica var. Citrata Leaf; LEMON PEEL; SOYBEAN OIL; Citric Acid Monohydrate; Potassium Sorbate; Sodium Benzoate

Yes to® Natural Man Broad Spectrum SPF 15 Face Lotion

DRUG FACTS

Active Ingredients

Zinc Oxide (3.2%), Titanium Dioxide (2.9%)

Purpose

Sunscreen

Uses

Helps prevent sunburn.

Warnings

For external use only

- Do not use on damaged or broken skin

- When using this product, avoid contact with eyes
- If contact occurs, rinse with water to remove

- Stop use and ask a doctor if rash or irritation develops and lasts

- Keep out of reach of children; if swallowed, get medical help or contact a Poison Control Center immediately.

Directions

Apply liberally 15 minutes before sun exposure. Use a water resistant sunscreen if swimming or sweating. Reapply at least every two hours. Children under 6 months: Ask a doctor.

Sun Protection Measure

Spending time in the sun increases your risk of skin cancer and early skin aging. To decrease the risk, regularly use a sunscreen with Broad Spectrum SPF value of 15 or higher and other sun protection measures including: Limit time in the sun, especially from 10am – 2pm. Wear long sleeved shirts, pants, hats and sun-glasses.

Inactive Ingredients

Water, Ethylhexyl Palmitate, Polyglyceryl-10 Distearate, Glycerin, Cetyl Acetate, Cocos Nucifera (Coconut) Oil [Certified Organic Ingredient] , Lecithin, Propanediol, Butyrospermum Parkii (Shea) Butter, Olea Europaea (Olive) Fruit Oil, Squalane, Theobroma Cacao (Cocoa) Seed Butter, Aloe Barbadensis (Aloe) Leaf Juice, Citrus Aurantifolia (Lime) Peel Extract, Citrus Aurantium Dulcis (Orange) Peel Extract, Citrus Grandis (Grapefruit) Peel Extract, Citrus Limon (Lemon) Peel Extract, Mentha Citrata Leaf Extract, Glycine Soya (Soybean) Oil, Microcrystalline Cellulose, Cetyl Alcohol, Aluminum Hydroxide, Xanthan Gum, Hydrated Silica, Cellulose Gum, Triethoxycaprylylsilane, Tocopherol, Citric Acid, Potassium Sorbate, Sodium Benzoate, Phenoxyethanol, Fragrance.

Other information

Protect the product in this container from excessive heat and direct sun.

PRINCIPAL DISPLAY PANEL - 50 mL Bottle Label

yesto®

NATURAL MAN

BROAD SPECTRUM
SPF 15
FACE LOTION

SOOTHING ALOE

Yes to™ men who moisturize.
This daily lightweight, matte
finish lotion is formulated
with moisturizing aloe and
mineral sunscreens for broad
spectrum protection.

NATURAL
95%
INGREDIENTS

1.7 fl oz / 50 mL